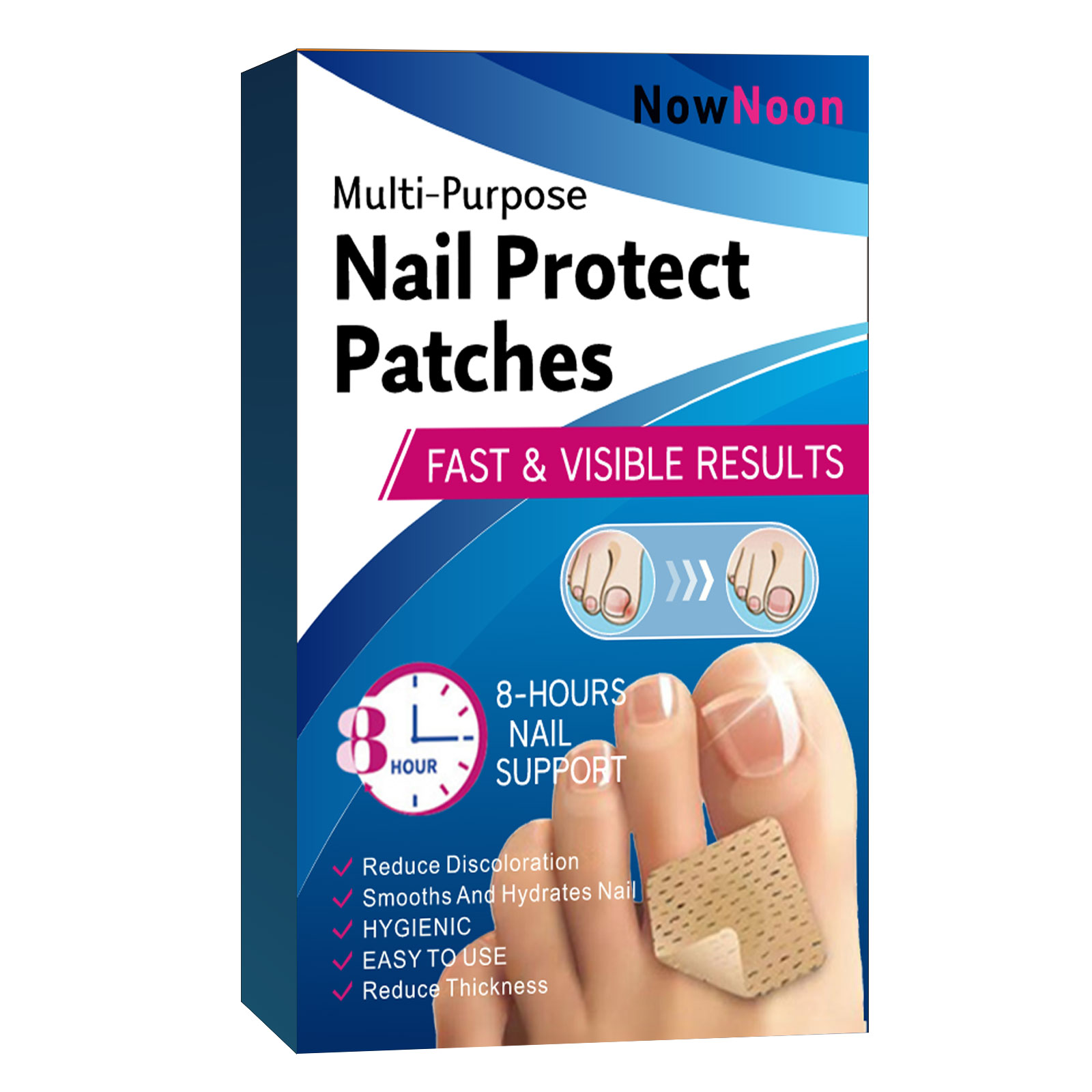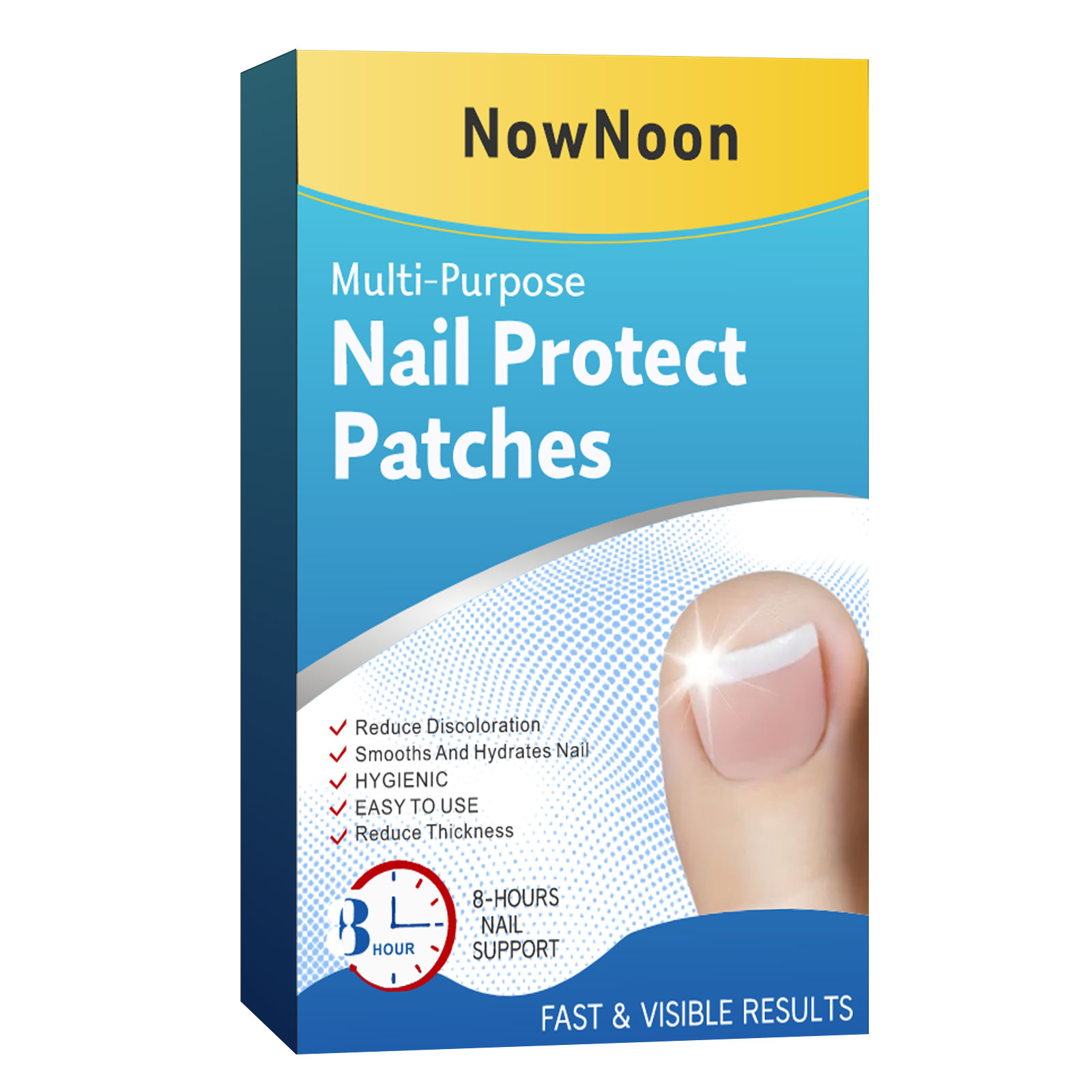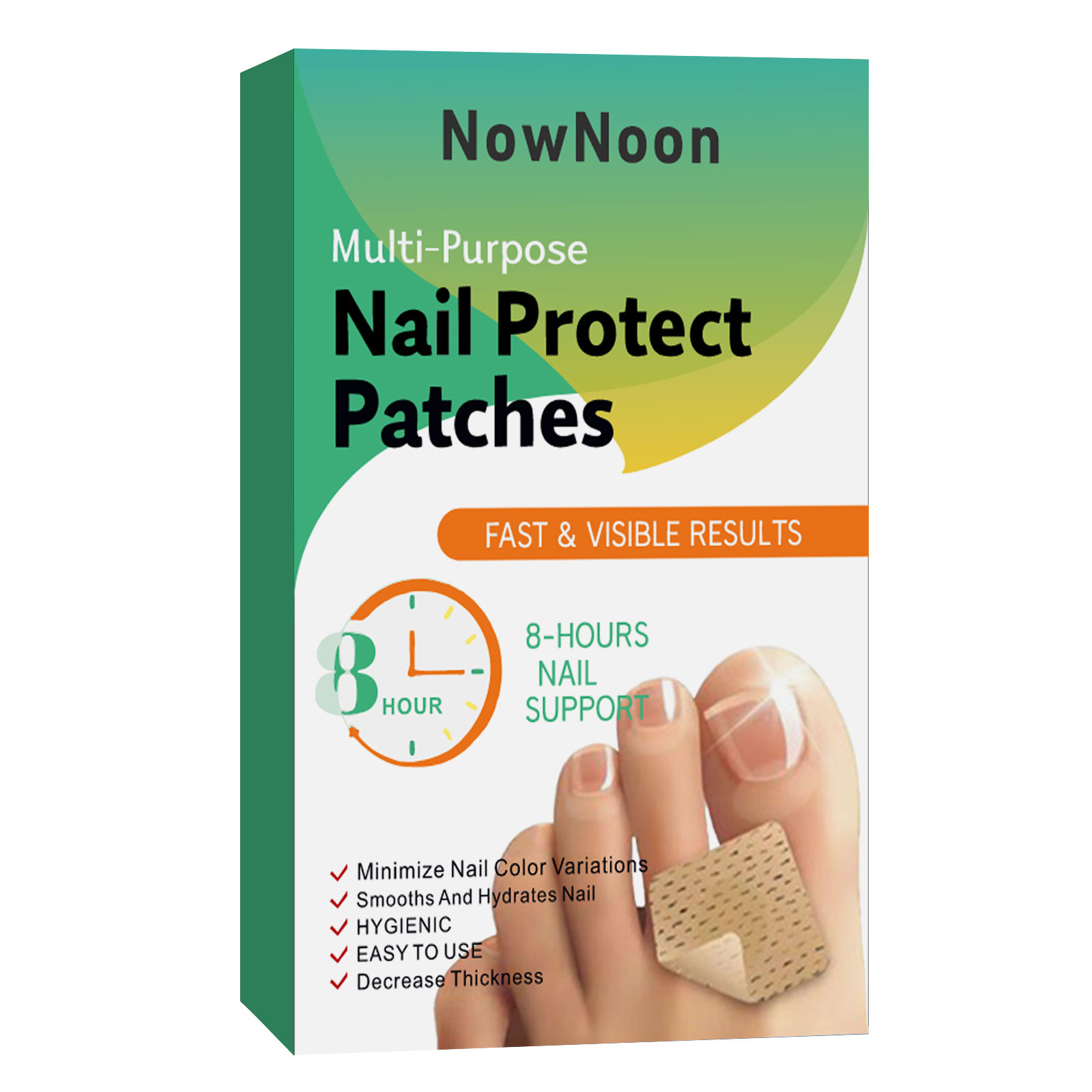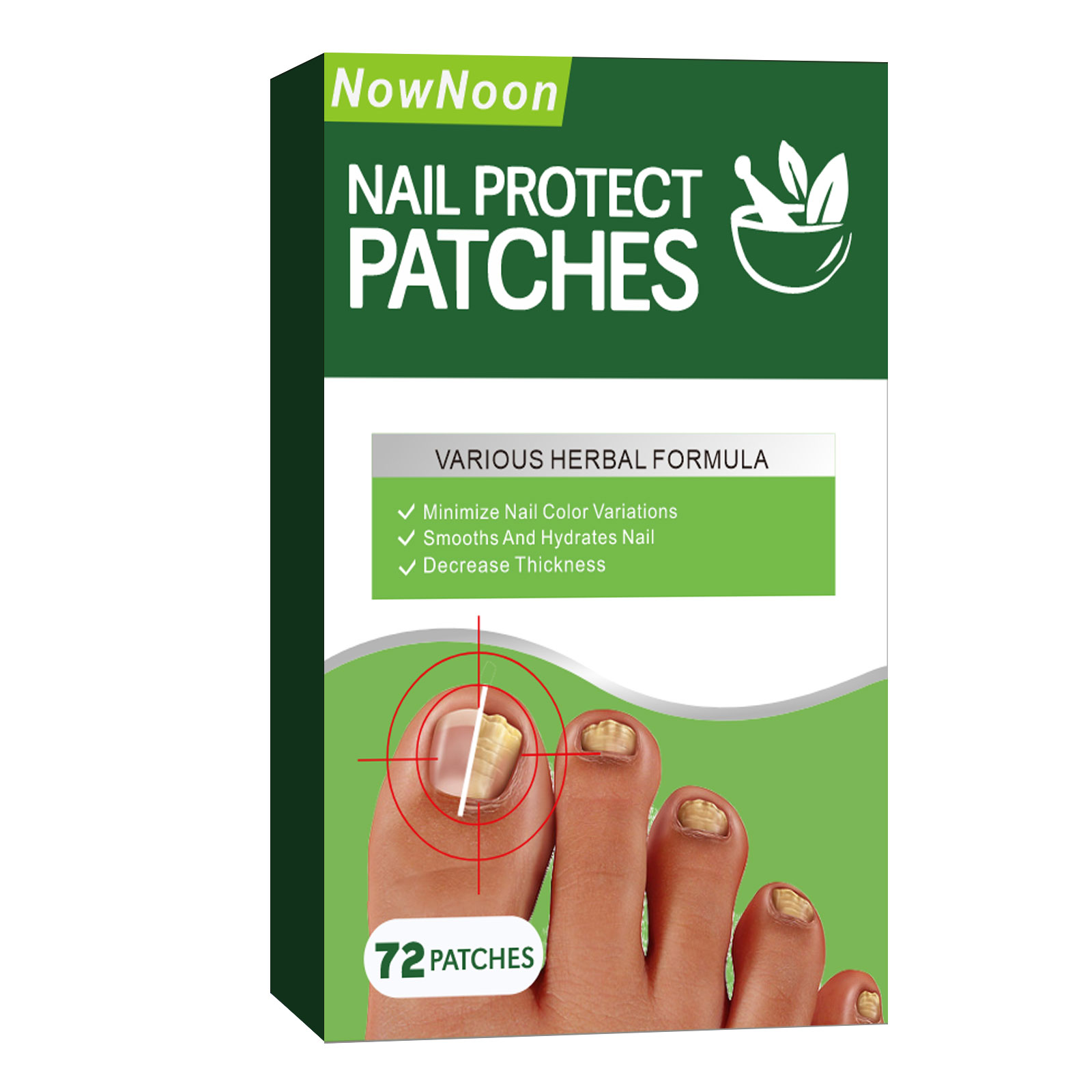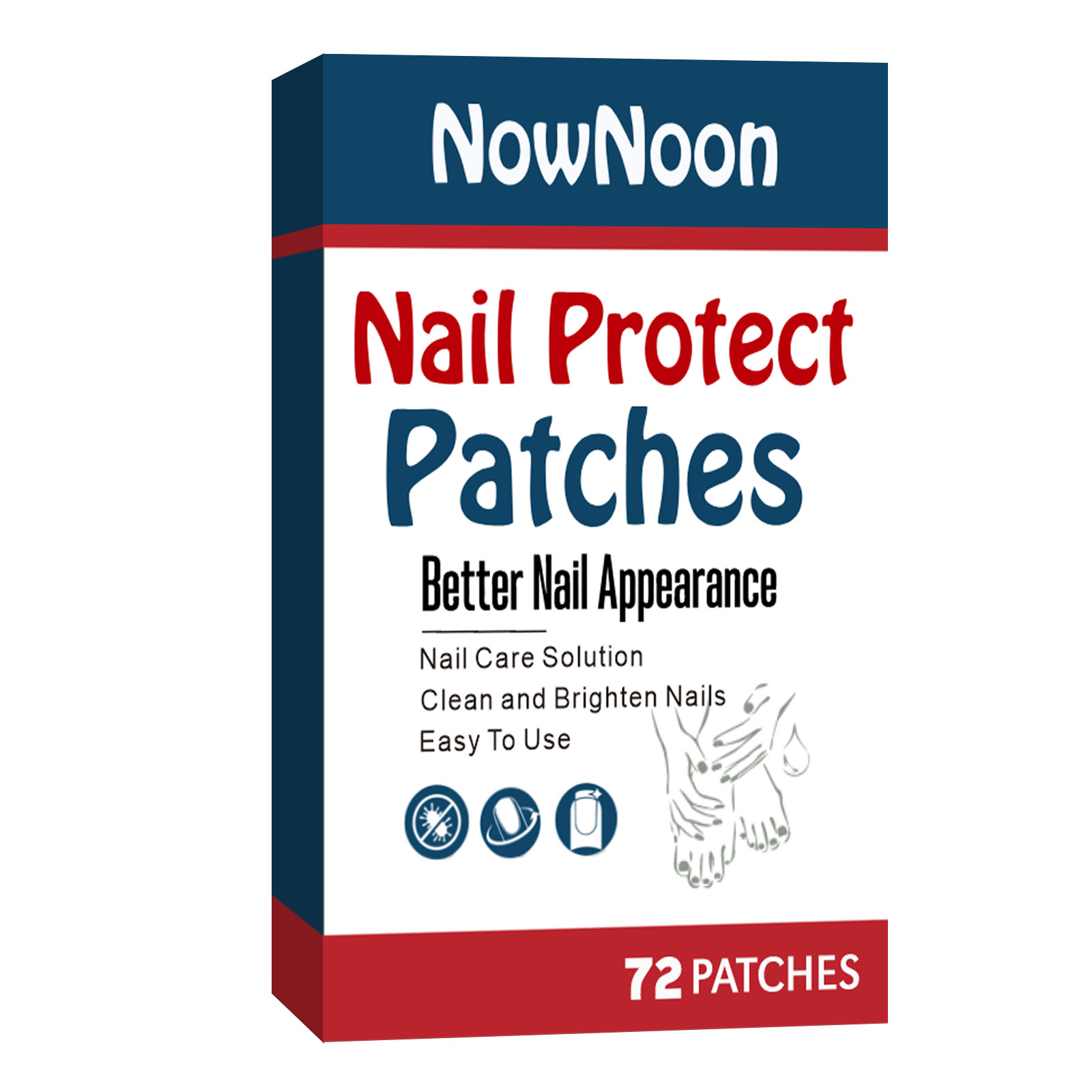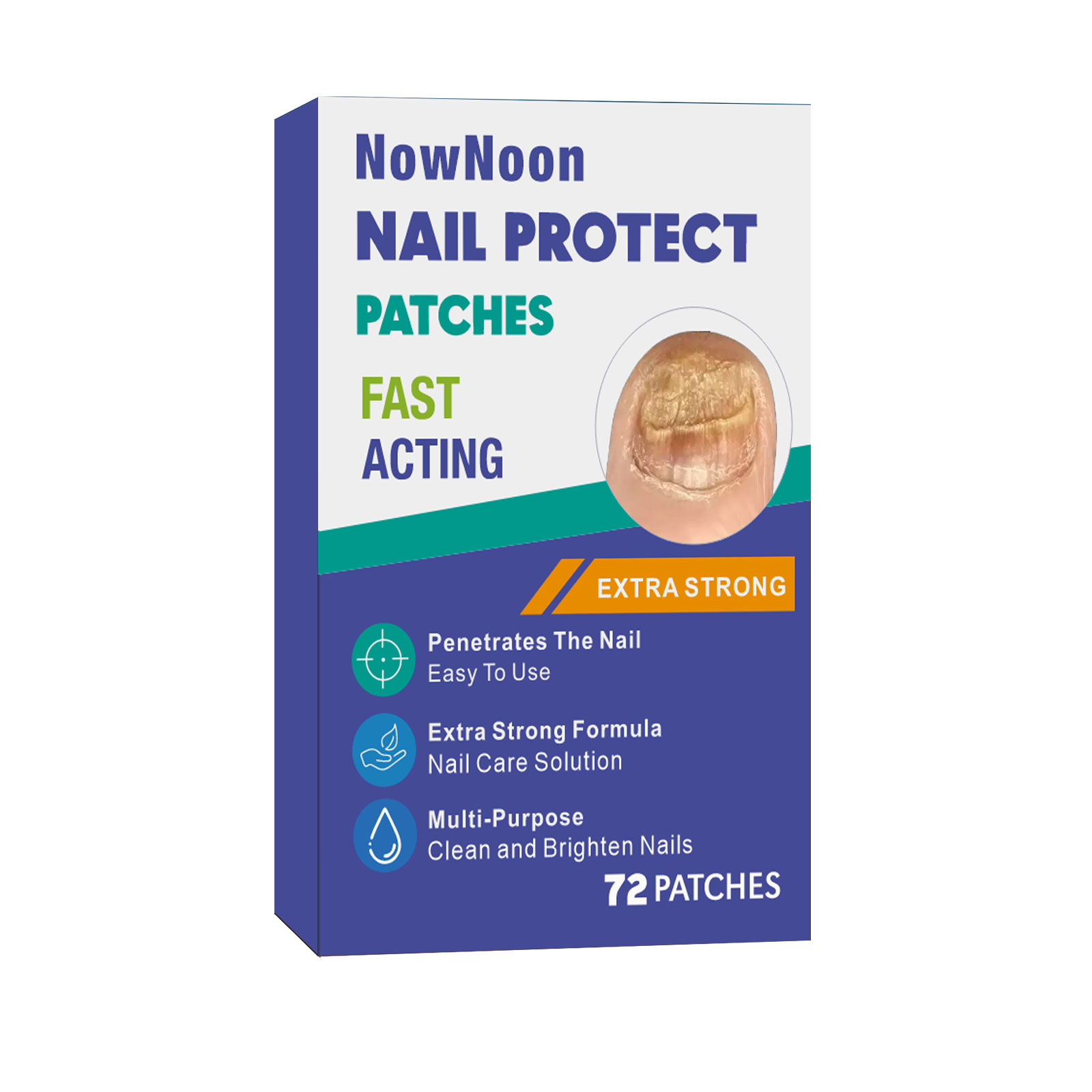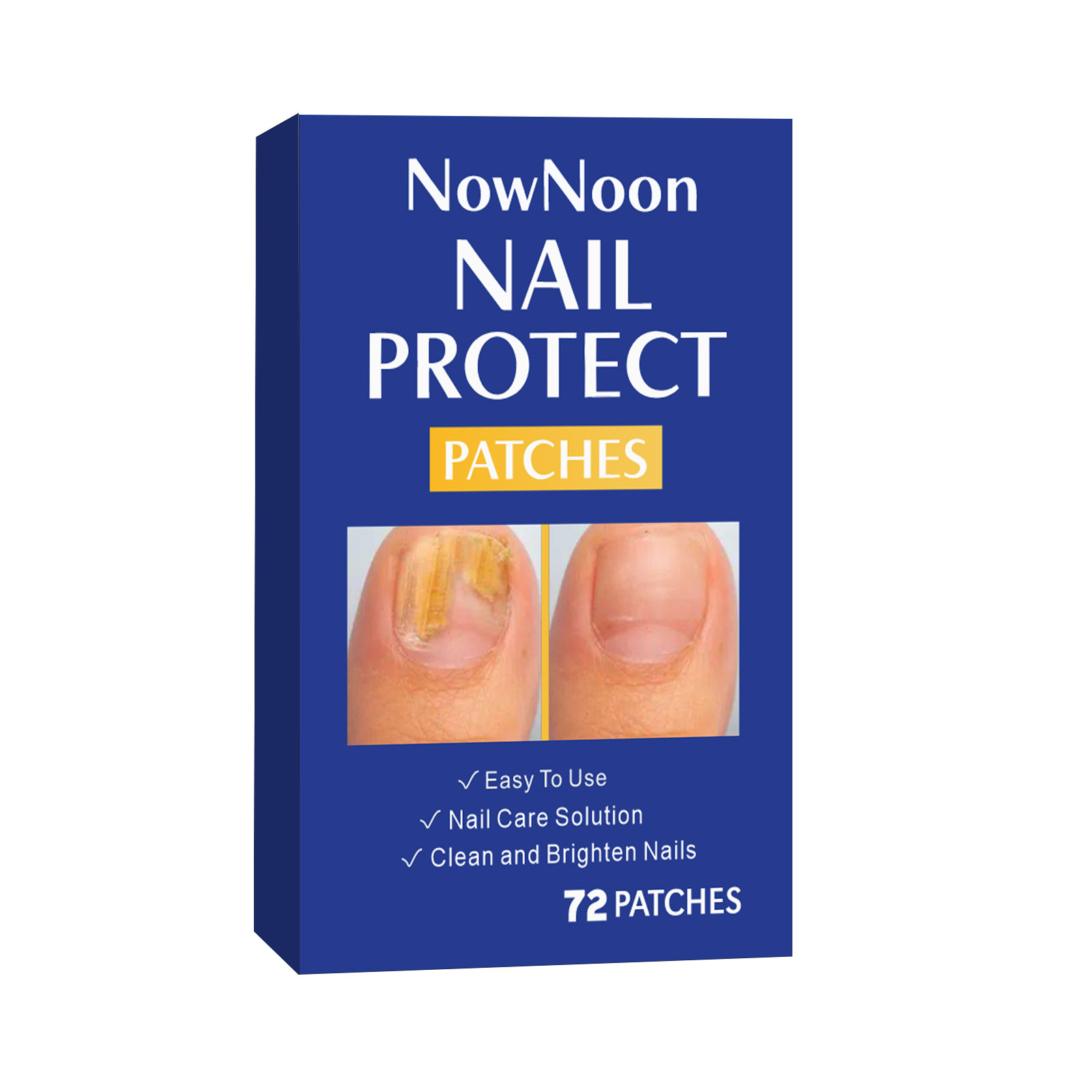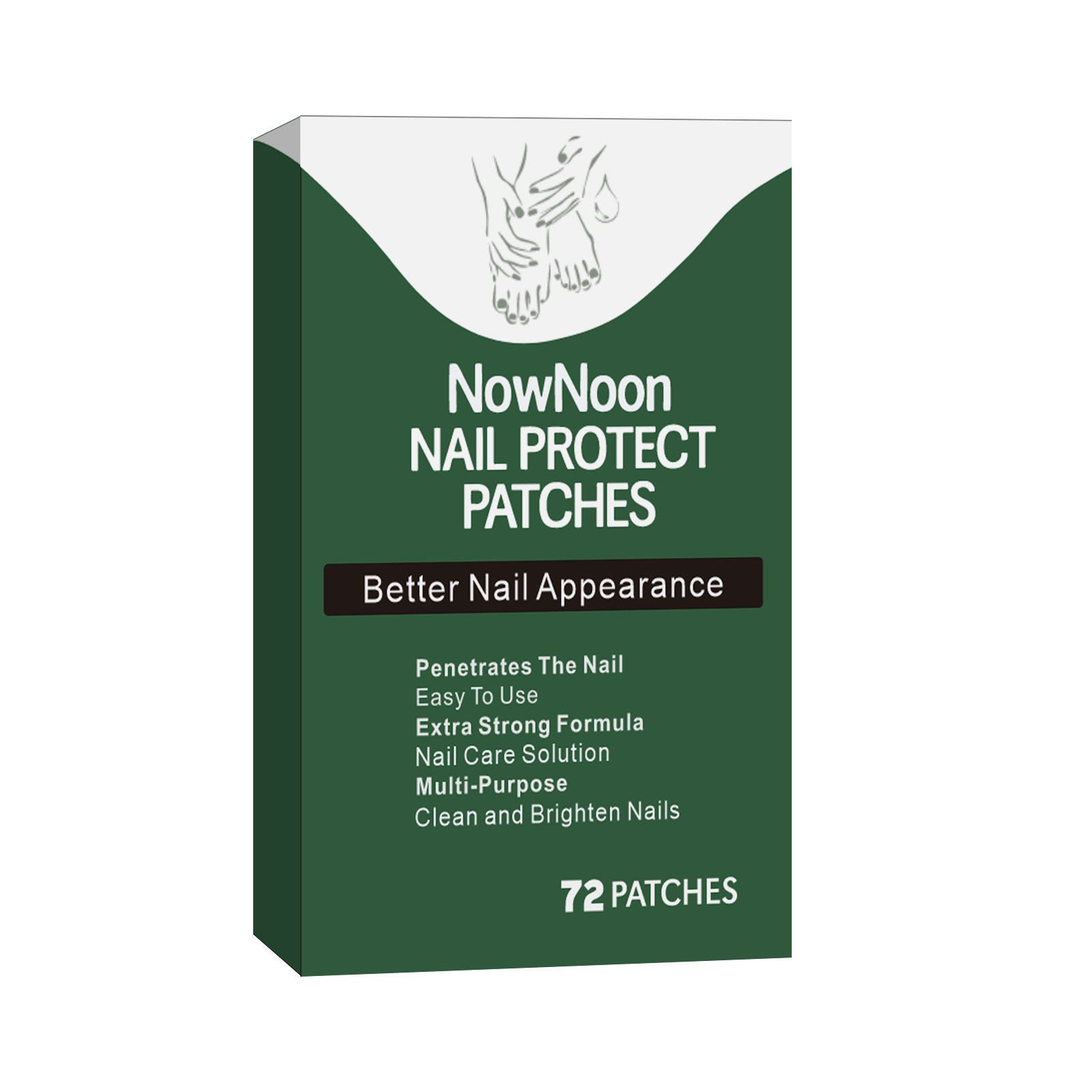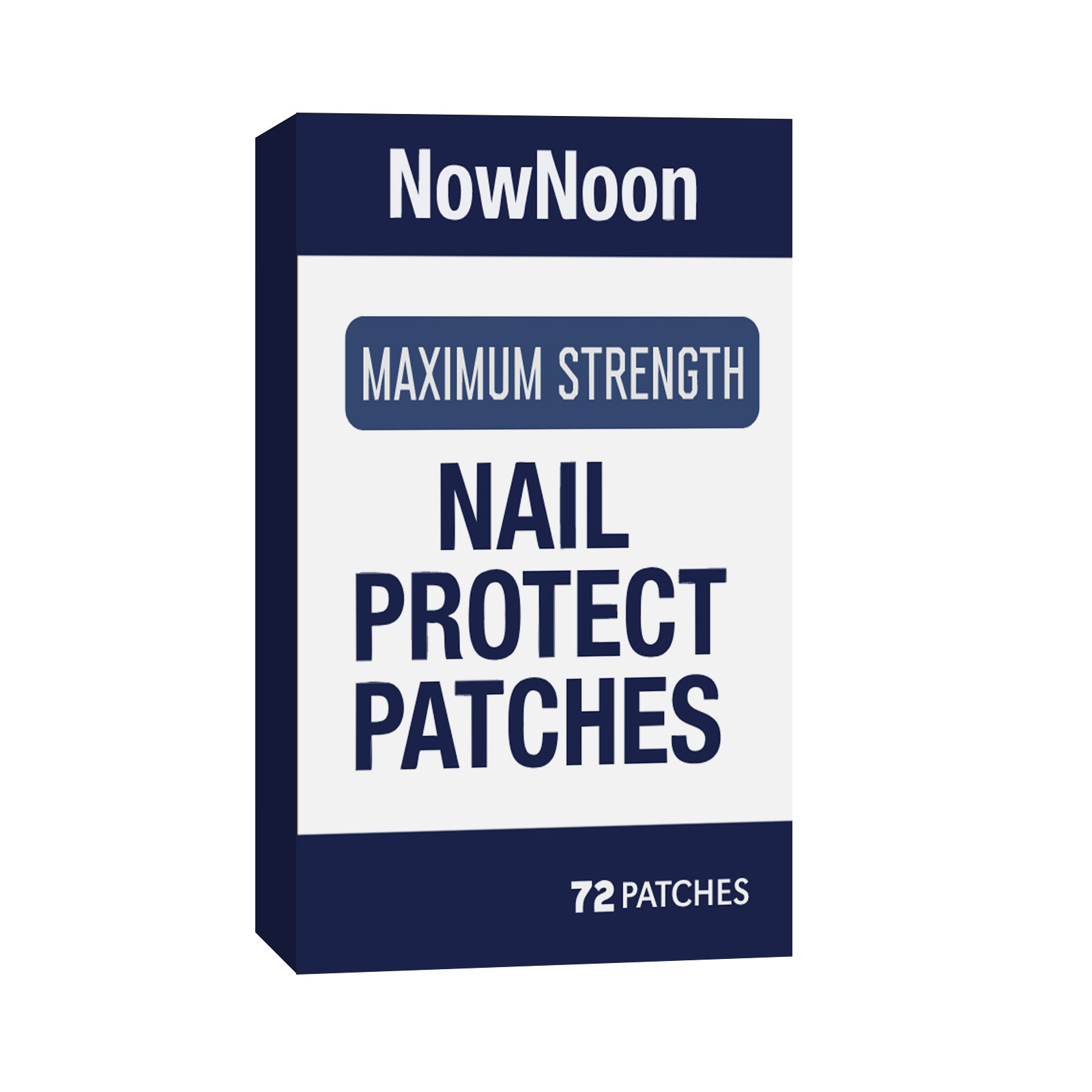 DRUG LABEL: NowNoon Nail Protect Patches
NDC: 84037-0101 | Form: PATCH
Manufacturer: Guangzhou Zhicunxiu Cosmetics Co., Ltd
Category: otc | Type: HUMAN OTC DRUG LABEL
Date: 20240801

ACTIVE INGREDIENTS: ACRYLATES CROSSPOLYMER-6 5 mg/1 1
INACTIVE INGREDIENTS: WATER

NowNoon Nail Protect Patches

Active Ingredients

Salicylic acid 0.5%

Purpose

Acne treatment

Uses

- treats and helps prevent acne

Warnings

For external use only

When using this product

keep away from eyes, lips and mouth. lf contact occurs, flush thoroughly with water.

skin irritation and dryness is more likely to occur if you use another topical acne medication at the same time If irritation occurs, only use one topical acne medication at a time.

Keep out of reach of children.

lf pregnant or breast-feeding,ask a healthcare professional before use. lf accidental ingestion and adverse reaction occurs, get medical help or contact a Poison Control Center.

Directions

- cleanse skin thoroughly before applying this product
- apply patch(es) to affected area(s)
- to remove, gently peel back patch and discard
- because excessive drying of the skin may occur, start with 1 application daily, then gradually increase to 2 or 3 times daily if needed or as directed by a doctor
- if bothersome dryness or peeling occurs, reduce application to once a day or every other day

Other information

store in a cool dry place, away from direct sunlight.

Inactive Ingredients

Acrylates copolymer, Ethyl acetate

Questions?

Email-us zcunxiu@163.com